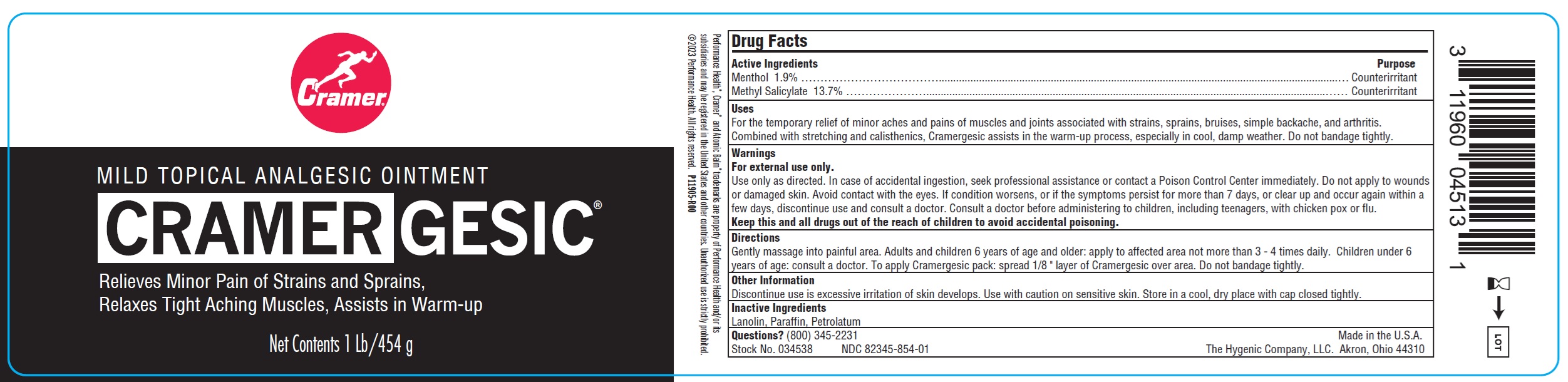 DRUG LABEL: Cramergesic
NDC: 82345-854 | Form: OINTMENT
Manufacturer: The Hygenic Company, LLC
Category: otc | Type: HUMAN OTC DRUG LABEL
Date: 20251013

ACTIVE INGREDIENTS: MENTHOL 19 mg/1 g; METHYL SALICYLATE 137 mg/1 g
INACTIVE INGREDIENTS: LANOLIN; PARAFFIN; PETROLATUM

Cramergesic

Active Ingredients

Menthol 1.9%

Methyl Salicylate 13.7%

Purpose

Counterirritant

Uses

For the temporary relief of minor aches and pains of muscles and joints associated with strains, sprains, bruises, simple backache, and arthritis.
Combined with stretching and calisthenics, Cramergesic assists in the warm-up process, especially in cool, damp weather. Do not bandage tightly.

Warnings

For external use only.

Use only as directed. In case of accidental ingestion, seek professional assistance or contact a Poison Control Center immediately. Do not apply to wounds or damaged skin. Avoid contact with the eyes. If condition worsens, or if the symptoms persist for more than 7 days, or clear up and occur again within a few days, discontinue use and consult a doctor.

Consult a doctor

before administering to children, including teenagers, with chicken pox or flu.

Keep this and all drugs out of the reach of children

to avoid accidental poisoning.

Directions

Gently massage into painful area. Adults and children 6 years of age and older: apply to affected area not more than 3 - 4 times daily. Children under 6 years of age: consult a doctor. To apply Cramergesic pack: spread 1/8 " layer of Cramergesic over area. Do not bandage tightly.

Other Information

Discontinue use is excessive irritation of skin develops. Use with caution on sensitive skin. Store in a cool, dry place with cap closed tightly.

Inactive Ingredients

Lanolin, Paraffin, Petrolatum

Questions?

(800) 345-2231